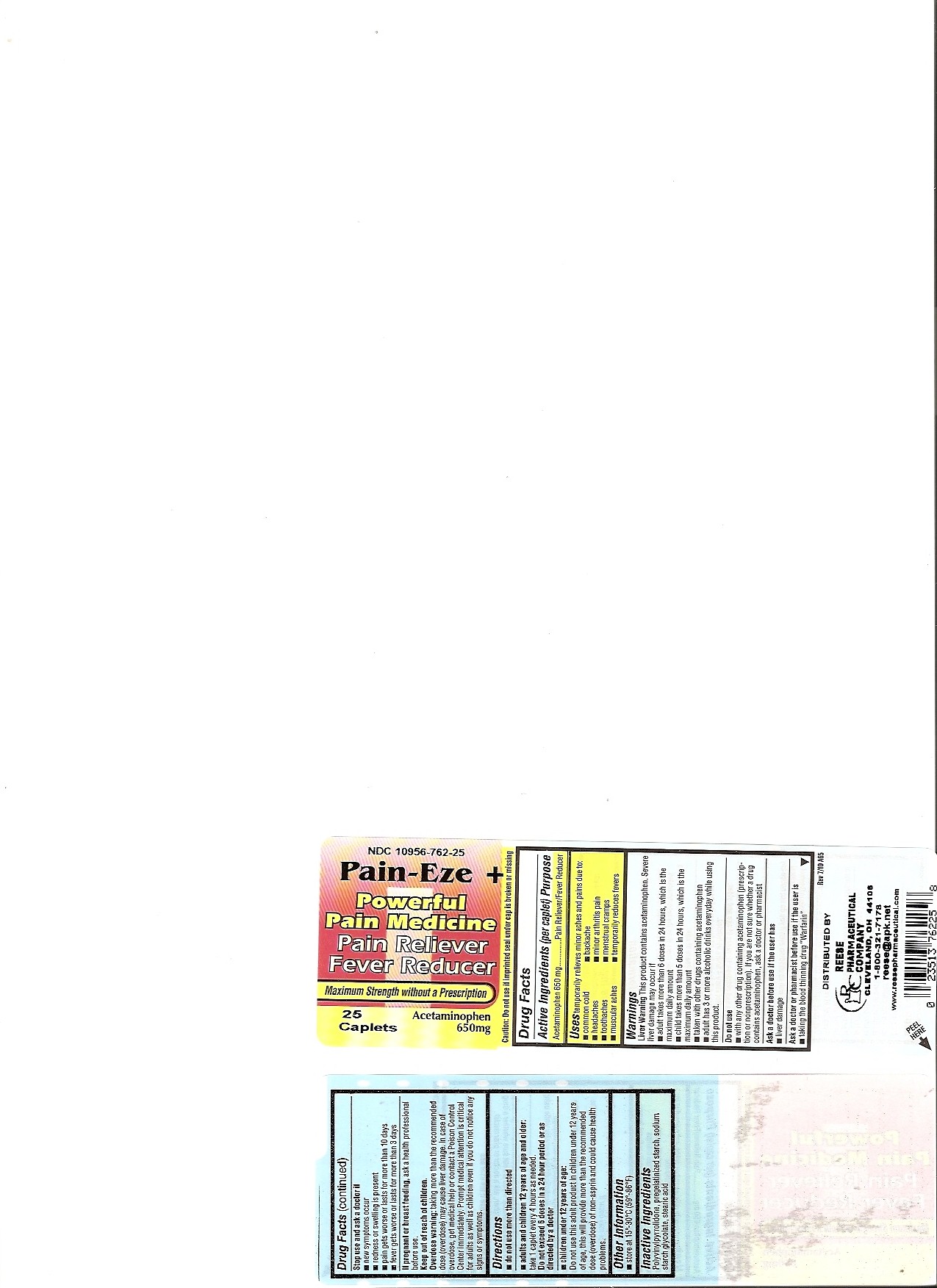 DRUG LABEL:  Powerful Pain Medicine
NDC: 10956-762 | Form: TABLET
Manufacturer: REESE PHARMACEUTICAL CO.
Category: otc | Type: HUMAN OTC DRUG LABEL
Date: 20101020

ACTIVE INGREDIENTS: Acetaminophen 650 mg/1 1
INACTIVE INGREDIENTS: STARCH, PREGELATINIZED CORN; STEARIC ACID

DRUG FACTS

ACTIVE INGREDIENT

Acetaminophen; 650 mg

PURPOSE

Acetaminophen 650 mg ; pain reliever ; fever reducer

keep out of reach of children.

INDICATIONS AND USAGE

temporarily relieves minor aches and pains due to

common cold ; headaches ; toothaches ; muscular aches ;

backache ; minor arthritis pain ; menstrual cramps ; temporarily reduces fevers

WARNINGS

LIVER WARNING This product contains acetaminophen.
severe liver damage may occur if adult takes more than 6 doses in 24 hours
which is the maximum daily amount.
child takes more than 5 doses in 24 hours
which is the maximum daily amount.
taken with other drugs containing acetaminophen.
adult has 3 or more alcoholic drinks everyday while using this product.

Directions

do not use more than directed

adults and children 12 years of age and older take 1 caplet

every 4 hours as needed.

do not exceed 6 doses in a 24 hour period or as directed by a doctor.

children under 12 years of age;

do not use this adult product in children under 12 years of age

this will provide more than the recommended dose (overdose) of

non aspirin and could cause health problems.

INACTIVE INGREDIENT

polyvinylpyrrolidone ; pregelaatinized starch ; sodium starch glycolate ;

stearic acid.